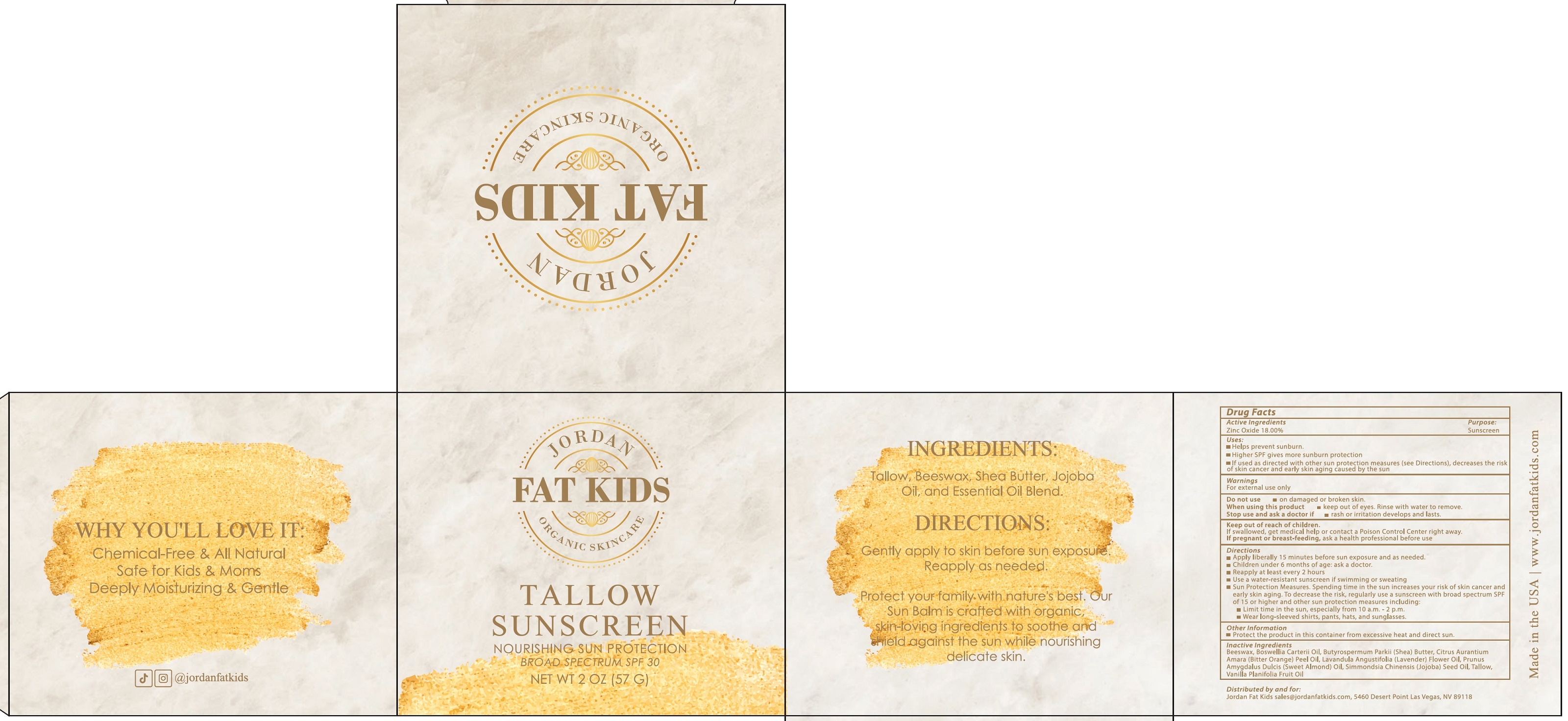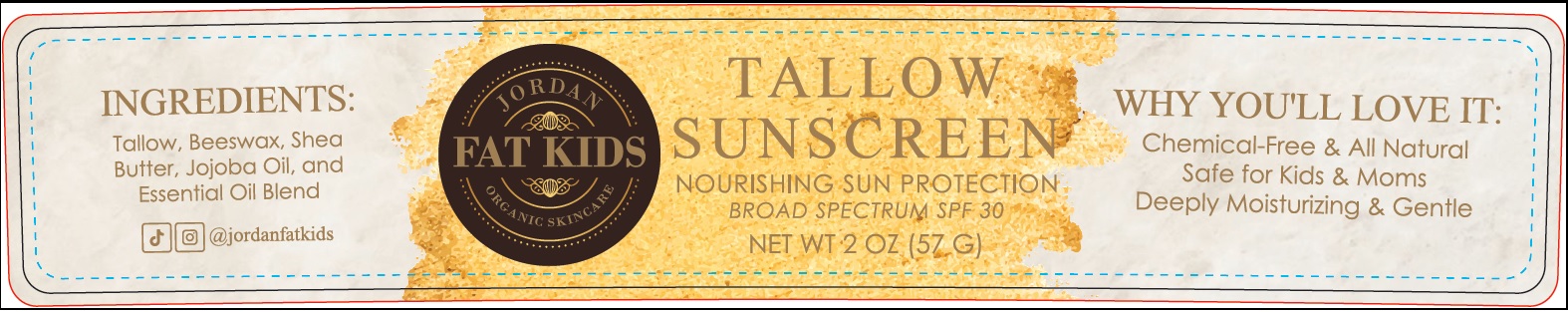 DRUG LABEL: JORDAN FAT KIDS Tallow Sunscreen SPF 30
NDC: 85979-630 | Form: OINTMENT
Manufacturer: JORDAN FAT KIDS LLC
Category: otc | Type: HUMAN OTC DRUG LABEL
Date: 20250804

ACTIVE INGREDIENTS: ZINC OXIDE 180 mg/1 g
INACTIVE INGREDIENTS: BEESWAX; BOSWELLIA CARTERII OIL; SHEA BUTTER; BITTER ORANGE OIL; ALMOND OIL; JOJOBA OIL

JORDAN FAT KIDS Tallow Sunscreen SPF 30

Active Ingredients

Zinc Oxide 18.00%

Purpose

Sunscreen

Uses:

- Helps prevent sunburn
- Higher SPF gives more sunburn protection
- If used as directed with other sun protection measures (see Directions), decreases the risk of skin cancer and early skin aging caused by the sun

Warnings

For extern al use only

Do not use

- on damaged or broken skin.

When using this product

- keep out of eyes. Rinse with water to remove.

Stop use and ask a doctor if

- rash or irritation develops and lasts.

Keep out of reach of children.

If swallowed, get medical help or contact a Poison Control Center right away.

If pregnant or breast-feeding,

ask a health professional before use

Directions:

• Apply liberally 15 minutes before sun exposure and as needed.
• Children under 6 months of age: ask a doctor.
• Reapply at least every 2 hours
• Use a water-resistant sunscreen if swimming or sweating
• Sun Protection Measures. Spending time in the sun increases your risk of skin cancer and early skin aging. To decrease the risk, regularly use a sunscreen with broad spectrum SPF of 15 or higher and other sun protection measures including:
• Limit time in the sun, especially from 10 a.m.-2 p.m.
• Wear long-sleeved shirts, pants, hats, and sunglasses.

Other information

- Protect the product in this container from excessive heat and direct sun.

Inactive ingredients

Beeswax, Boswellia Carterii Oil, Butyrospermum Parkii (Shea) Butter, Citrus Aurantium Amara (Bitter Orange) Peel Oil, Lavandula Angustifolia (Lavender) Flower Oil, Prunus Amygdalus Dulcis (Sweet Almond) Oil, Simmondsia Chinensis (Jojoba) Seed Oil, Tallow Vanilla Planifolia Fruit Oil